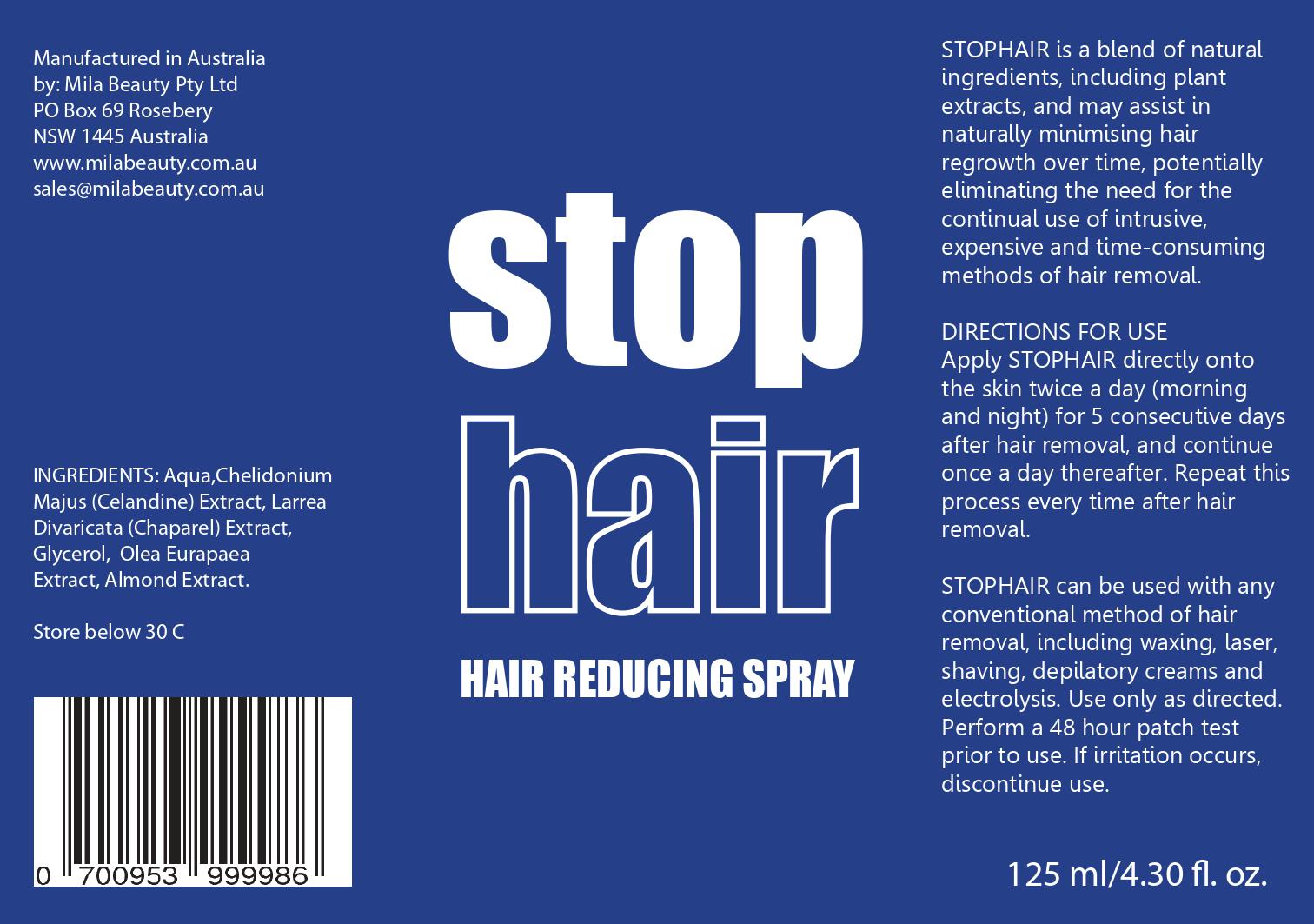 DRUG LABEL: stop hair
NDC: 50965-001 | Form: SPRAY
Manufacturer: MILA BEAUTY PTY LTD
Category: otc | Type: HUMAN OTC DRUG LABEL
Date: 20211007

ACTIVE INGREDIENTS: CITRIC ACID MONOHYDRATE 7 mg/1 mL
INACTIVE INGREDIENTS: GLYCERIN; WATER; ALMOND

STOP HAIR

ACTIVE INGREDIENT

Citric Acid Monohydrate 7mg/ml (0.7 % w/v)

Purpose

DEPILATORY/HAIR INHIBITOR

Keep Out of Reach of Children.

Indication and Usage

DEPILATORY/HAIR INHIBITOR

DOSAGE AND ADMINISTRATION

Directions for Use

Apply STOPHAIR directly onto the skin twice a day (morning and night) for 5 consecutive days after hair removal, and continue once a day thereafter. Repeat this process every time after hair removal.

Inactive Ingredient

Water, Almond Extract and Glycerine

WARNINGS

For external use only.